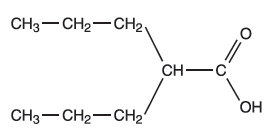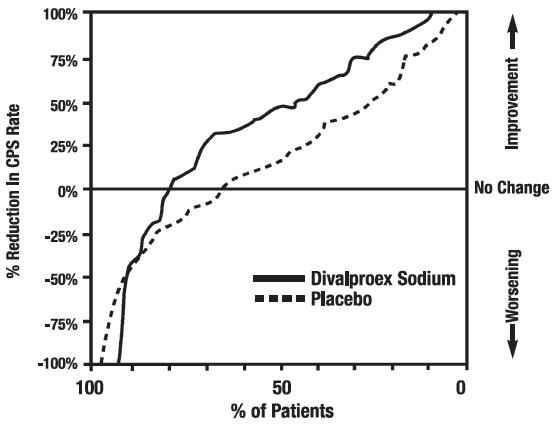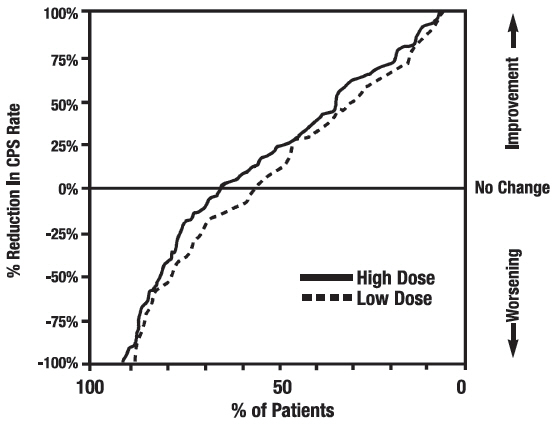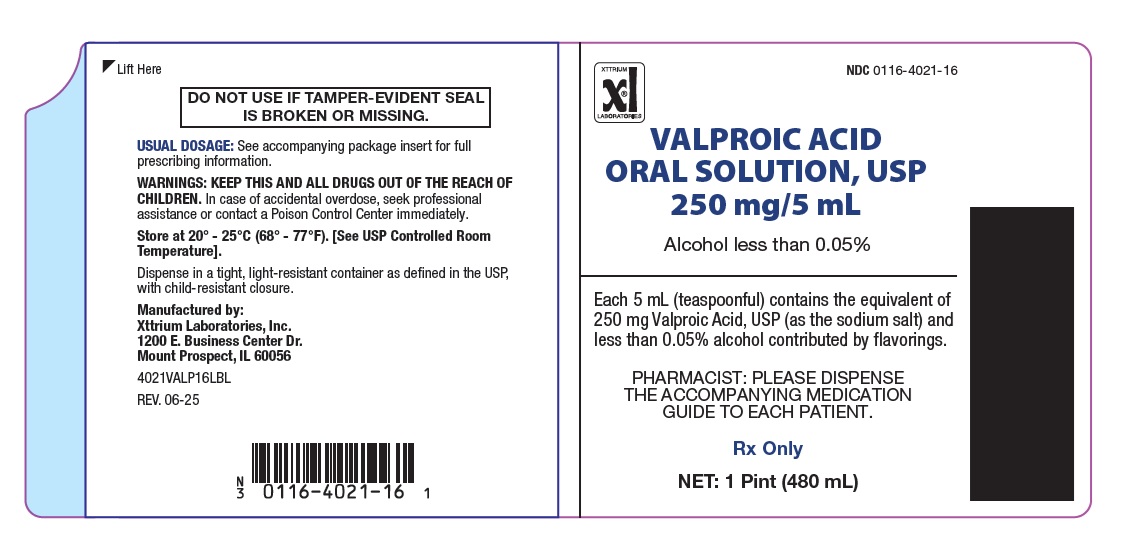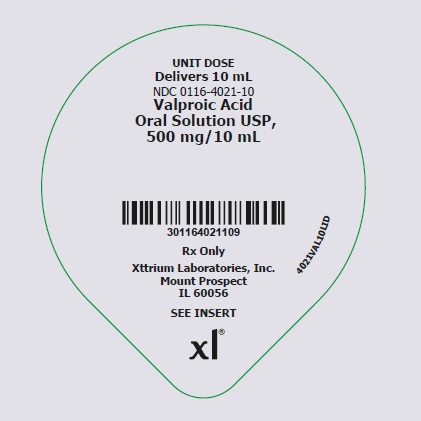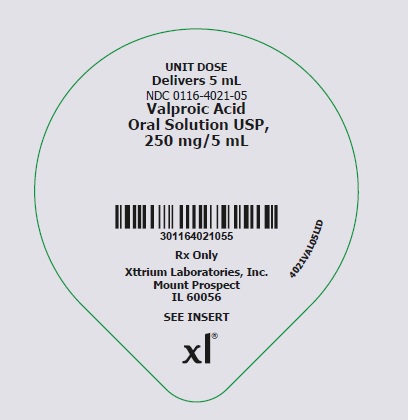 DRUG LABEL: Valproic Acid
NDC: 0116-4021 | Form: SOLUTION
Manufacturer: Xttrium Laboratories Inc.
Category: prescription | Type: HUMAN PRESCRIPTION DRUG LABEL
Date: 20250729

ACTIVE INGREDIENTS: VALPROIC ACID 250 mg/5 mL
INACTIVE INGREDIENTS: PRUNUS SEROTINA (WILD CHERRY) BARK; GLYCERIN; PROPYLENE GLYCOL; WATER; FD&C RED NO. 40; SODIUM BENZOATE; POTASSIUM PHOSPHATE, DIBASIC; CORN SYRUP; METHYLPARABEN; SODIUM HYDROXIDE; HYDROCHLORIC ACID; SUCROSE; ALCOHOL; CHERRY

These highlights do not include all the information needed to use Valproic Acid Oral Solution safely and effectively. See full
prescribing information for Valproic Acid Oral Solution.
Valproic Acid Oral Solution, USP
Initial U.S. Approval: 1978

HIGHLIGHTS OF PRESCRIBING INFORMATION

These highlights do not include all the information needed to use Valproic Acid Oral Solution safely and effectively.
See full prescribing information for Valproic Acid Oral Solution.
Valproic Acid Oral Solution, USP
Initial U.S. Approval: 1978

WARNINGS: LIFE THREATENING ADVERSE REACTIONS

See full prescribing information for complete boxed warning.
• Hepatotoxicity, including fatalities, usually during the first 6 months of treatment. Children under the age of two
years and patients with mitochondrial disorders are at higher risk. Monitor patients closely, and perform serum
liver testing prior to therapy and at frequent intervals thereafter (5.1)
• Fetal Risk, particularly neural tube defects, other major malformations, and decreased IQ (5.2, 5.3, 5.4)
• Pancreatitis, including fatal hemorrhagic cases (5.5)

1 INDICATIONS AND USAGE

Valproic Acid Oral Solution is indicated for:

Monotherapy and adjunctive therapy of complex partial seizures; sole and adjunctive therapy of simple and complex absence seizures; adjunctive therapy in patients with multiple seizure types that include absence seizures (1)

2 DOSAGE AND ADMINISTRATION

Valproic Acid Oral Solution is intended for oral administration. (2.1)

Simple and Complex Absence Seizures: Start at 10 to 15 mg/kg/day, increasing at 1 week intervals by 5 to 10 mg/kg/week until seizure control or limiting side effects (2.1)
Safety of doses above 60 mg/kg/day is not established (2.1, 2.2)

3 DOSAGE FORMS AND STRENGTH

Oral Solution: Equivalent of 250 mg valproic acid per 5 mL as the sodium salt

4 CONTRAINDICATIONS

- Hepatic disease or significant hepatic dysfunction (4, 5.1)
- Known mitochondrial disorders caused by mutations in mitochondrial DNA polymerase γ (POLG) (4, 5.1)
- Suspected POLG-related disorder in children under two years of age (4, 5.1)
- Known hypersensitivity to the drug (4, 5.12)
- Urea cycle disorders (4, 5.6)
- Prophylaxis of migraine headaches: Pregnant women , women of child bearing potential not using effective contraception (4, 8.1)

5 WARNINGS AND PRECAUTIONS

- Hepatotoxicity; evaluate high risk populations and monitor serum liver tests (5.1)

• Birth defects, decreased IQ, and neurodevelopmental disorders following in utero exposure; should not be used to treat
women with epilepsy or bipolar disorder who are pregnant or who plan to become pregnant or to treat a woman of
childbearing potential unless other medications have failed to provide adequate symptom control or are otherwise
unacceptable (5.2, 5.3, 5.4)
• Pancreatitis; Valproic Acid Oral Solution should ordinarily be discontinued (5.5)
• Suicidal behavior or ideation; Antiepileptic drugs, including Valproic Acid Oral Solution, increase the risk of suicidal thoughts
or behavior (5.7)

- Bleeding and other hematopoietic disorders; monitor platelet counts and coagulation tests (5.8) Hyperammonemia and

hyperammonemic encephalopathy; measure ammonia level if unexplained lethargy and vomiting or changes in mental
status, and also with concomitant topiramate use; consider discontinuation of valproate therapy (5.6, 5.9, 5.10)
• Hypothermia; Hypothermia has been reported during valproate therapy with or without associated hyperammonemia. This
adverse reaction can also occur in patients using concomitant topiramate (5.11)
• Drug Reaction with Eosinophilia and Systemic Symptoms (DRESS)/Multiorgan hypersensitivity reaction; discontinue Valproic
Acid Oral Solution (5.12)
• Somnolence in the elderly can occur. Valproic Acid Oral Solution dosage should be increased slowly and with regular
monitoring for fluid and nutritional intake (5.14)

6 ADVERSE REACTIONS

• Most common adverse reactions (reported >5%) are abdominal pain, alopecia, amblyopia/blurred vision, amnesia,
anorexia, asthenia, ataxia, bronchitis, constipation, depression, diarrhea, diplopia, dizziness, dyspepsia, dyspnea,
ecchymosis, emotional lability, fever, flu syndrome, headache, increased appetite, infection, insomnia, nausea,
nervousness, nystagmus, peripheral edema, pharyngitis, rhinitis, somnolence, thinking abnormal, thrombocytopenia,
tinnitus, tremor, vomiting, weight gain, weight loss. (6.1)
• The safety and tolerability of valproate in pediatric patients were shown to be comparable to those in adults (8.4).
To report SUSPECTED ADVERSE REACTIONS, contact Xttrium Laboratories, Inc. at 1-800-587-3721 or FDA at
1-800-FDA-1088 or www.fda.gov/medwatch

7 DRUG INTERACTIONS

• Hepatic enzyme-inducing drugs (e.g., phenytoin, carbamazepine, phenobarbital, primidone, rifampin) can increase
valproate clearance, while enzyme inhibitors (e.g., felbamate) can decrease valproate clearance. Therefore increased
monitoring of valproate and concomitant drug concentrations and dosage adjustment are indicated whenever
enzyme-inducing or inhibiting drugs are introduced or withdrawn (7.1)
• Aspirin, carbapenem antibiotics, estrogen-containing hormonal contraceptives: Monitoring of valproate concentrations is
recommended (7.1)
• Co-administration of valproate can affect the pharmacokinetics of other drugs (e.g. diazepam, ethosuximide, lamotrigine,
phenytoin) by inhibiting their metabolism or protein binding displacement (7.2)
• Patients stabilized on rufinamide should begin valproate therapy at a low dose, and titrate to clinically effective dose (7.2)
• Dosage adjustment of amitriptyline/nortriptyline, propofol, warfarin, and zidovudine may be necessary if used
concomitantly with Valproic Acid Oral Solution (7.2)
• Topiramate: Hyperammonemia and encephalopathy (5.10, 7.3)

8 USE IN SPECIFIC POPULATIONS

• Pregnancy: Valproic Acid Oral Solution can cause congenital malformations including neural tube defects, decreased IQ, and
neurodevelopmental disorders (5.2, 5.3, 8.1)
• Pediatric: Children under the age of two years are at considerably higher risk of fatal hepatotoxicity (5.1, 8.4)
• Geriatric: Reduce starting dose; increase dosage more slowly; monitor fluid and nutritional intake, and somnolence (5.14,
8.5)

10 OVERDOSAGE

Overdosage with valproate may result in somnolence, heart block, deep coma, and hypernatremia. Fatalities have been reported; however, patients have recovered from valproate levels as high as 2,120 mcg/mL.

In overdose situations, the fraction of drug not bound to protein is high and hemodialysis or tandem hemodialysis plus hemoperfusion may result in significant removal of drug. The benefit of gastric lavage or emesis will vary with the time since ingestion. General supportive measures should be applied with particular attention to the maintenance of adequate urinary output.

Naloxone has been reported to reverse the CNS depressant effects of valproate overdosage. Because naloxone could theoretically also reverse the antiepileptic effects of valproate, it should be used with caution in patients with epilepsy.

11 DESCRIPTION

Valproic acid is a carboxylic acid designated as 2-propylpentanoic acid. It is also known as dipropylacetic acid. Valproic acid has the following structure:

Valproic acid (pKa 4.8) has a molecular weight of 144 and occurs as a colorless liquid with a characteristic odor. It is slightly soluble in water (1.3 mg/mL) and very soluble in organic solvents.

Valproic Acid Oral Solution is an antiepileptic for oral administration. The oral solution contains the equivalent of 250 mg valproic acid per 5 mL as the sodium salt.

Inactive Ingredients

alcohol (less than 0.05%), artificial cherry flavor, artificial wild cherry flavor, corn syrup solids, FD&C Red No. 40, glycerin, hydrochloric acid, liquid sugar, methylparaben, potassium phosphate dibasic, propylene glycol, purified water, sodium benzoate and sodium hydroxide. The pH range is between 7.0 and 8.0.

12 CLINICAL PHARMACOLOGY

12.1 Mechanism of Action

Valproic acid dissociates to the valproate ion in the gastrointestinal tract. The mechanisms by which valproate exerts its therapeutic effects have not been established. It has been suggested that its activity in epilepsy is related to increased brain concentrations of gamma-aminobutyric acid (GABA).

12.2 Pharmacodynamics

The relationship between plasma concentration and clinical response is not well documented. One contributing factor is the nonlinear, concentration dependent protein binding of valproate which affects the clearance of the drug. Thus, monitoring of total serum valproate cannot provide a reliable index of the bioactive valproate species.

For example, because the plasma protein binding of valproate is concentration dependent, the free fraction increases from approximately 10% at 40 mcg/mL to 18.5% at 130 mcg/mL. Higher than expected free fractions occur in the elderly, in hyperlipidemic patients, and in patients with hepatic and renal diseases.

Epilepsy

The therapeutic range in epilepsy is commonly considered to be 50 to 100 mcg/mL of total valproate, although some patients may be controlled with lower or higher plasma concentrations.

12.3 Pharmacokinetics

Absorption/Bioavailability

Equivalent oral doses of divalproex sodium products and valproic acid capsules deliver equivalent quantities of valproate ion systemically. Although the rate of valproate ion absorption may vary with the formulation administered (liquid, solid, or sprinkle), conditions of use (e.g., fasting or postprandial) and the method of administration (e.g., whether the contents of the capsule are sprinkled on food or the capsule is taken intact), these differences should be of minor clinical importance under the steady state conditions achieved in chronic use in the treatment of epilepsy.

However, it is possible that differences among the various valproate products in Tmax and Cmax could be important upon initiation of treatment. For example, in single dose studies, the effect of feeding had a greater influence on the rate of absorption of the divalproex sodium tablet (increase in Tmax from 4 to 8 hours) than on the absorption of the divalproex sodium sprinkle capsules (increase in Tmax from 3.3 to 4.8 hours).

While the absorption rate from the G.I. tract and fluctuation in valproate plasma concentrations vary with dosing regimen and formulation, the efficacy of valproate as an anticonvulsant in chronic use is unlikely to be affected. Experience employing dosing regimens from once-a-day to four-times-a-day, as well as studies in primate epilepsy models involving constant rate infusion, indicate that total daily systemic bioavailability (extent of absorption) is the primary determinant of seizure control and that differences in the ratios of plasma peak to trough concentrations between valproate formulations are inconsequential from a practical clinical standpoint.

Co-administration of oral valproate products with food and substitution among the various divalproex sodium and valproic acid formulations should cause no clinical problems in the management of patients with epilepsy [see Dosage and Administration (2.1) ] . Nonetheless, any changes in dosage administration, or the addition or discontinuance of concomitant drugs should ordinarily be accompanied by close monitoring of clinical status and valproate plasma concentrations.

Distribution

Protein Binding

The plasma protein binding of valproate is concentration dependent and the free fraction increases from approximately 10% at 40 mcg/mL to 18.5% at 130 mcg/mL. Protein binding of valproate is reduced in the elderly, in patients with chronic hepatic diseases, in patients with renal impairment, and in the presence of other drugs (e.g., aspirin). Conversely, valproate may displace certain protein-bound drugs (e.g., phenytoin, carbamazepine, warfarin, and tolbutamide). [see Drug Interactions (7.2) for more detailed information on the pharmacokinetic interactions of valproate with other drugs].

CNS Distribution

Valproate concentrations in cerebrospinal fluid (CSF) approximate unbound concentrations in plasma (about 10% of total concentration).

Metabolism

Valproate is metabolized almost entirely by the liver. In adult patients on monotherapy, 30–50% of an administered dose appears in urine as a glucuronide conjugate. Mitochondrial β-oxidation is the other major metabolic pathway, typically accounting for over 40% of the dose. Usually, less than 15–20% of the dose is eliminated by other oxidative mechanisms. Less than 3% of an administered dose is excreted unchanged in urine.

The relationship between dose and total valproate concentration is nonlinear; concentration does not increase proportionally with the dose, but rather, increases to a lesser extent due to saturable plasma protein binding. The kinetics of unbound drug are linear.

Elimination

Mean plasma clearance and volume of distribution for total valproate are 0.56 L/hr/1.73 m^2 and 11 L/1.73 m^2, respectively. Mean plasma clearance and volume of distribution for free valproate are 4.6 L/hr/1.73 m^2 and 92 L/1.73 m^2. Mean terminal half-life for valproate monotherapy ranged from 9 to 16 hours following oral dosing regimens of 250 to 1,000 mg.

The estimates cited apply primarily to patients who are not taking drugs that affect hepatic metabolizing enzyme systems. For example, patients taking enzyme-inducing antiepileptic drugs (carbamazepine, phenytoin, and phenobarbital) will clear valproate more rapidly. Because of these changes in valproate clearance, monitoring of antiepileptic concentrations should be intensified whenever concomitant antiepileptics are introduced or withdrawn.

Special Populations

Effect of Age

Neonates

Children within the first two months of life have a markedly decreased ability to eliminate valproate compared to older children and adults. This is a result of reduced clearance (perhaps due to delay in development of glucuronosyltransferase and other enzyme systems involved in valproate elimination) as well as increased volume of distribution (in part due to decreased plasma protein binding). For example, in one study, the half-life in children under 10 days ranged from 10 to 67 hours compared to a range of 7 to 13 hours in children greater than 2 months.

Children

Pediatric patients (i.e., between 3 months and 10 years) have 50% higher clearances expressed on weight (i.e., mL/min/kg) than do adults. Over the age of 10 years, children have pharmacokinetic parameters that approximate those of adults.

Elderly

The capacity of elderly patients (age range: 68 to 89 years) to eliminate valproate has been shown to be reduced compared to younger adults (age range: 22 to 26 years). Intrinsic clearance is reduced by 39%; the free fraction is increased by 44%. Accordingly, the initial dosage should be reduced in the elderly [see Dosage and Administration (2.2)] .

Effect of Sex

There are no differences in the body surface area adjusted unbound clearance between males and females (4.8 ± 0.17 and 4.7 ± 0.07 L/hr per 1.73 m^2, respectively).

Effect of Race

The effects of race on the kinetics of valproate have not been studied.

Effect of Disease

Liver Disease

Liver disease impairs the capacity to eliminate valproate. In one study, the clearance of free valproate was decreased by 50% in 7 patients with cirrhosis and by 16% in 4 patients with acute hepatitis, compared with 6 healthy subjects. In that study, the half-life of valproate was increased from 12 to 18 hours. Liver disease is also associated with decreased albumin concentrations and larger unbound fractions (2 to 2.6 fold increase) of valproate. Accordingly, monitoring of total concentrations may be misleading since free concentrations may be substantially elevated in patients with hepatic disease whereas total concentrations may appear to be normal. [see Boxed Warning, Contraindications (4), and Warnings and Precautions (5.1)] .

Renal Disease

A slight reduction (27%) in the unbound clearance of valproate has been reported in patients with renal failure (creatinine clearance < 10 mL/minute); however, hemodialysis typically reduces valproate concentrations by about 20%. Therefore, no dosage adjustment appears to be necessary in patients with renal failure. Protein binding in these patients is substantially reduced; thus, monitoring total concentrations may be misleading.

13 NONCLINICAL TOXICOLOGY

13.1 Carcinogenesis, Mutagenesis, and Impairment of Fertility

Carcinogenesis

Valproate was administered orally to rats and mice at doses of 80 and 170 mg/kg/day (less than the maximum recommended human dose on a mg/m^2 basis) for two years. The primary findings were an increase in the incidence of subcutaneous fibrosarcomas in high-dose male rats receiving valproate and a dose-related trend for benign pulmonary adenomas in male mice receiving valproate.

Mutagenesis

Valproate was not mutagenic in an in vitro bacterial assay (Ames test), did not produce dominant lethal effects in mice, and did not increase chromosome aberration frequency in an in vivo cytogenetic study in rats. Increased frequencies of sister chromatid exchange (SCE) have been reported in a study of epileptic children taking valproate, but this association was not observed in another study conducted in adults.

Impairment of Fertility

In chronic toxicity studies in juvenile and adult rats and dogs, administration of valproate resulted in testicular atrophy and reduced spermatogenesis at oral doses of 400 mg/kg/day or greater in rats (approximately equal to or greater than the maximum recommended human dose (MRHD) on a mg/m^2 basis) and 150 mg/kg/day or greater in dogs (approximately equal to or greater than the MRHD on a mg/m^2 basis). Fertility studies in rats have shown no effect on fertility at oral doses of valproate up to 350 mg/kg/day (approximately equal to the MRHD on a mg/m^2 basis) for 60 days.

14 CLINICAL STUDIES

The studies described in the following section were conducted using divalproex sodium tablets.

14.1 Epilepsy

The efficacy of divalproex sodium in reducing the incidence of complex partial seizures (CPS) that occur in isolation or in association with other seizure types was established in two controlled trials.

In one, multi-clinic, placebo controlled study employing an add-on design (adjunctive therapy), 144 patients who continued to suffer eight or more CPS per 8 weeks during an 8 week period of monotherapy with doses of either carbamazepine or phenytoin sufficient to assure plasma concentrations within the "therapeutic range" were randomized to receive, in addition to their original antiepilepsy drug (AED), either divalproex sodium or placebo. Randomized patients were to be followed for a total of 16 weeks. The following table presents the findings.

Table 5. Adjunctive Therapy Study Median Incidence of CPS per 8 Weeks
Add-on Treatment | Number of Patients | Baseline Incidence | Experimental Incidence
Divalproex sodium | 75 | 16.0 | 8.9 [Reduction from baseline statistically significantly greater for divalproex sodium than placebo at p ≤ 0.05 level.]
Placebo | 69 | 14.5 | 11.5

Figure 1 presents the proportion of patients (X axis) whose percentage reduction from baseline in complex partial seizure rates was at least as great as that indicated on the Y axis in the adjunctive therapy study. A positive percent reduction indicates an improvement (i.e., a decrease in seizure frequency), while a negative percent reduction indicates worsening. Thus, in a display of this type, the curve for an effective treatment is shifted to the left of the curve for placebo. This figure shows that the proportion of patients achieving any particular level of improvement was consistently higher for divalproex sodium than for placebo. For example, 45% of patients treated with divalproex sodium had a ≥ 50% reduction in complex partial seizure rate compared to 23% of patients treated with placebo.

Figure 1

The second study assessed the capacity of divalproex sodium to reduce the incidence of CPS when administered as the sole AED. The study compared the incidence of CPS among patients randomized to either a high or low dose treatment arm. Patients qualified for entry into the randomized comparison phase of this study only if 1) they continued to experience 2 or more CPS per 4 weeks during an 8 to 12 week long period of monotherapy with adequate doses of an AED (i.e., phenytoin, carbamazepine, phenobarbital, or primidone) and 2) they made a successful transition over a two week interval to divalproex sodium. Patients entering the randomized phase were then brought to their assigned target dose, gradually tapered off their concomitant AED and followed for an interval as long as 22 weeks. Less than 50% of the patients randomized, however, completed the study. In patients converted to divalproex sodium monotherapy, the mean total valproate concentrations during monotherapy were 71 and 123 mcg/mL in the low dose and high dose groups, respectively.

The following table presents the findings for all patients randomized who had at least one post-randomization assessment.

Table 6. Monotherapy Study Median Incidence of CPS per 8 Weeks
Treatment | Number of Patients | Baseline Incidence | Randomized Phase Incidence
High dose divalproex sodium | 131 | 13.2 | 10.7 [Reduction from baseline statistically significantly greater for high dose than low dose at p ≤ 0.05 level.]
Low dose divalproex sodium | 134 | 14.2 | 13.8

Figure 2 presents the proportion of patients (X axis) whose percentage reduction from baseline in complex partial seizure rates was at least as great as that indicated on the Y axis in the monotherapy study. A positive percent reduction indicates an improvement (i.e., a decrease in seizure frequency), while a negative percent reduction indicates worsening. Thus, in a display of this type, the curve for a more effective treatment is shifted to the left of the curve for a less effective treatment. This figure shows that the proportion of patients achieving any particular level of reduction was consistently higher for high dose divalproex sodium than for low dose divalproex sodium. For example, when switching from carbamazepine, phenytoin, phenobarbital or primidone monotherapy to high dose divalproex sodium monotherapy, 63% of patients experienced no change or a reduction in complex partial seizure rates compared to 54% of patients receiving low dose divalproex sodium.

Figure 2

Information on pediatric studies is presented in section 8.

15 REFERENCES

^1Meador KJ, Baker GA, Browning N, et al. Fetal antiepileptic drug exposure and cognitive outcomes at age 6 years (NEAD study): a prospective observational study. Lancet Neurology 2013; 12 (3):244–252.

16 HOW SUPPLIED/STORAGE AND HANDLING

Valproic Acid Oral Solution, USP is available as a clear, cherry-flavored red oral solution containing the equivalent of 250 mg of valproic acid per 5 mL as the sodium salt in the following oral dosage forms:

16 fl oz (473 mL) bottles (NDC 0116-4021-16).

5 mL unit dose cups (NDC 0116-4021-05) packaged in trays of 10 unit dose cups each with either 4 or 10 trays to a case

10 mL unit dose cups (NDC 0116-4021-10) packaged in trays of 10 unit dose cups each with 10 trays to a case

RECOMMENDED STORAGE

Store at 20°–25°C (68°–77°F) [See USP Controlled Room Temperature]. Dispense in a tight, light-resistant container as defined in the USP, with child-resistant closure.

17 PATIENT COUNSELING INFORMATION

Advise the patient to read the FDA-approved patient labeling (Medication Guide).

Hepatotoxicity

Warn patients and guardians that nausea, vomiting, abdominal pain, anorexia, diarrhea, asthenia, and/or jaundice can be symptoms of hepatotoxicity and, therefore, require further medical evaluation promptly [see Warnings and Precautions (5.1) ].

Pancreatitis

Warn patients and guardians that abdominal pain, nausea, vomiting, and/or anorexia can be symptoms of pancreatitis and, therefore, require further medical evaluation promptly [see Warnings and Precautions (5.5)].

Birth Defects and Decreased IQ

Inform pregnant women and women of childbearing potential (including girls beginning the onset of puberty) that use of valproate during pregnancy increases the risk of birth defects and decreased IQ, and neurodevelopmental disorders in children who were exposed in utero. Advise women to use effective contraception while using valproate. When appropriate, counsel these patients about alternative therapeutic options. This is particularly important when valproate use is considered for a condition not usually associated with permanent injury or death such as prophylaxis of migraine headache [ see Contraindications (4)].Advise patients to read the Medication Guide, which appears as the last section of the labeling [see Warnings and Precautions (5.2, 5.3, 5.4) and Use in Specific Populations (8.1)].

Pregnancy Registry:

Advise women of childbearing potential to discuss pregnancy planning with their doctor and to contact their doctor immediately if they think they are pregnant.

Encourage women who are taking valproic acid oral solution to enroll in the North American Antiepileptic Drug (NAAED) Pregnancy Registry if they become pregnant. This registry is collecting information about the safety of antiepileptic drugs during pregnancy. To enroll, patients can call the toll free number 1-888-233-2334 or visit the website, http://www.aedpregnancyregistry.org [see Use in Specific Populations (8.1)].

Suicidal Thinking and Behavior

Counsel patients, their caregivers, and families that AEDs, including valproic acid, may increase the risk of suicidal thoughts and behavior and to be alert for the emergence or worsening of symptoms of depression, any unusual changes in mood or behavior, or the emergence of suicidal thoughts, behavior, or thoughts about self-harm. Instruct patients, caregivers, and families to report behaviors of concern immediately to the healthcare providers [see Warnings and Precautions (5.7)].

Hyperammonemia

Inform patients of the signs and symptoms associated with hyperammonemic encephalopathy and to notify the prescriber if any of these symptoms occur [see Warnings and Precautions(5.9, 5.10) ].

CNS Depression

Since valproate products may produce CNS depression, especially when combined with another CNS depressant (e.g., alcohol), advise patients not to engage in hazardous activities, such as driving an automobile or operating dangerous machinery, until it is known that they do not become drowsy from the drug.

Multiorgan Hypersensitivity Reactions

Instruct patients that a fever associated with other organ system involvement (rash, lymphadenopathy, etc.) may be drug-related and should be reported to the physician immediately [see Warnings and Precautions (5.12)].

MEDICATION GUIDE

Valproic Acid Oral Solution

Read this Medication Guide before you start taking valproic acid oral solution and each time you get a refill. There may be new information. This information does not take the place of talking to your healthcare provider about your medical condition or treatment.

What is the most important information I should know about valproic acid oral solution?

Do not stop taking valproic acid oral solution without first talking to your healthcare provider.

Stopping valproic acid oral solution suddenly can cause serious problems.

Valproic acid oral solution can cause serious side effects, including:

1. Serious liver damage that can cause death, especially in children younger than 2 years old.

The risk of getting this serious liver damage is more likely to happen within the first 6 months of treatment.

Call your healthcare provider right away if you get any of the following symptoms:

- nausea or vomiting that does not go away
- loss of appetite
- pain on the right side of your stomach (abdomen)
- dark urine
- swelling of your face
- yellowing of your skin or the whites of your eyes

In some cases, liver damage may continue despite stopping the drug.

2. Valproic acid oral solution may harm your unborn baby.

- If you take valproic acid oral solution during pregnancy for any medical condition, your baby is at risk for serious birth defects that affect the brain and spinal cord and are called spina bifida or neural tube defects. These defects occur in 1 to 2 out of every 100 babies born to mothers who use this medicine during pregnancy. These defects can begin in the first month, even before you know you are pregnant. Other birth defects that affect the structures of the heart, head, arms, legs, and the opening where the urine comes out (urethra) on the bottom of the penis can also happen. Decreased hearing or hearing loss can also happen.
- Birth defects may occur even in children born to women who are not taking any medicines and do not have other risk factors.
- Taking folic acid supplements before getting pregnant and during early pregnancy can lower the chance of having a baby with a neural tube defect.
- If you take valproic acid oral solution during pregnancy for any medical condition, your child is at risk for having a lower IQ and may be at risk for developing autism or attention deficit/hyperactivity disorder.
- There may be other medicines to treat your condition that have a lower chance of causing birth defects, decreased IQ, or other disorders in your child.
- Women who are pregnant must not take valproic acid oral solution to prevent migraine headaches.
- All women of child-bearing age (including girls from the start of puberty) should talk to their healthcare provider about using other possible treatments instead of valproic acid oral solution. If the decision is made to use valproic acid oral solution, you should use effective birth control (contraception).
- Tell your healthcare provider right away if you become pregnant while taking valproic acid oral solution. You and your healthcare provider should decide if you will continue to take valproic acid oral solution while you are pregnant.
- Pregnancy Registry: If you become pregnant while taking valproic acid oral solution, talk to your healthcare provider about registering with the North American Antiepileptic Drug Pregnancy Registry. You can enroll in this registry by calling toll-free 1-888-233-2334 or by visiting the website, http://www.aedpregnancyregistry.org/. The purpose of this registry is to collect information about the safety of antiepilectic drugs during pregnancy.

3. Inflammation of your pancreas that can cause death.

Call your healthcare provider right away if you have any of these symptoms:

- severe stomach pain that you may also feel in your back
- nausea or vomiting that does not go away

4. Like other antiepileptic drugs, valproic acid oral solution may cause suicidal thoughts or actions in a very small number of people, about 1 in 500.

Call a healthcare provider right away if you have any of these symptoms, especially if they are new, worse, or worry you:

- thoughts about suicide or dying
- attempts to commit suicide
- new or worse depression
- new or worse anxiety
- feeling agitated or restless
- panic attacks
- trouble sleeping (insomnia)
- new or worse irritability
- acting aggressive, being angry, or violent
- acting on dangerous impulses
- an extreme increase in activity and talking (mania)
- other unusual changes in behavior or mood

How can I watch for early symptoms of suicidal thoughts and actions?

- Pay attetion to any changes, especially sudden changes in mood, behaviors, thoughts, or feelings.
- Keep all follow-up visits with your healthcare provider as scheduled.

Call your healthcare provider between visits as needed, especially if you are worried about your symptoms.

Do not stop valproic acid oral solution without first talking to a healthcare provider. Stopping valproic acid oral solution suddenly can cause serious problems. Stopping a seizure medicine suddenly in a patient who has epilepsy can cause seizures that will not stop (status epilepticus).

Suicidal thoughts or actions can be caused by things other than medicines. If you have suicidal thoughts or actions, your healthcare provider may check for other causes.

What is valproic acid oral solution?

Valproic acid oral solution is a prescription medicine used alone or with other medicines, to treat:

- complex partial seizures in adults and children 10 years of age and older
- simple and complex absence seizures, with or without other seizure types

Who should not take valproic acid oral solution?

Do not take valproic acid oral solution if you:

- have liver problems
- have or think you have a genetic liver problem caused by a mitochondrial disorder (e.g. Alpers-Huttenlocher syndrome)
- are allergic to valproic acid, or any of the ingredients in valproic acid oral solution. See the end of this leaflet for a complete list of ingredients in valproic acid oral solution.
- have a genetic problem called urea cycle disorder
- are taking it to prevent migraine headaches and are either pregnant or may become pregnant because you are not using effective birth control (contraception)

What should I tell my healthcare provider before taking valproic acid oral solution?

Before you take valproic acid oral solution, tell your healthcare provider if you:

- have a genetic liver problem caused by a mitochondrial disorder (e.g. Alpers-Huttenlocher syndrome)
- drink alcohol
- are pregnant or breastfeeding. Valproic acid can pass into breast milk. Talk to your healthcare provider about the best way to feed your baby if you take valproic acid oral solution.
- have or have had depression, mood problems, or suicidal thoughts or behavior
- have any other medical conditions

Tell your healthcare provider about all the medicines you take, including prescription and non-prescription medicines, vitamins, herbal supplements and medicines that you take for a short period of time.

Taking valproic acid oral solution with certain other medicines can cause side effects or affect how well they work. Do not start or stop other medicines without talking to your healthcare provider.

Know the medicines you take. Keep a list of them and show it to your healthcare provider and pharmacist each time you get a new medicine.

How should I take valproic acid oral solution?

- Take valproic acid oral solution exactly as your healthcare provider tells you. Your healthcare provider will tell you how much valproic acid oral solution to take and when to take it.
- Your healthcare provider may change your dose.
- Do not change your dose of valproic acid oral solution without talking to your healthcare provider.
- Do not stop taking valproic acid oral solution without first talking to your healthcare provider. Stopping valproic acid oral solution suddenly can cause serious problems.
- If you take too much valproic acid oral solution, call your healthcare provider or local Poison Control Center right away.

What should I avoid while taking valproic acid oral solution?

- Valproic acid oral solution can cause drowsiness and dizziness. Do not drink alcohol or take other medicines that make you sleepy or dizzy while taking valproic acid oral solution, until you talk with your doctor. Taking valproic acid oral solution with alcohol or drugs that cause sleepiness or dizziness may make your sleepiness or dizziness worse.
- Do not drive a car or operate dangerous machinery until you know how valproic acid oral solution affects you. Valproic acid oral solution can slow your thinking and motor skills.

What are the possible side effects of valproic acid oral solution?

- See "What is the most important information I should know about valproic acid oral solution?"

Valproic acid oral solution can cause serious side effects including:

- Bleeding problems: red or purple spots on your skin, bruising, pain and swelling into your joints due to bleeding or bleeding from your mouth or nose.
- High ammonia levels in your blood: feeling tired, vomiting, changes in mental status.
- Low body temperature (hypothermia): drop in your body temperature to less than 95°F, feeling tired, confusion, coma.
- Allergic (hypersensitivity) reactions: fever, skin rash, hives, sores in your mouth, blistering and peeling of your skin, swelling of your lymph nodes, swelling of your face, eyes, lips, tongue, or throat, trouble swallowing or breathing.
- Drowsiness or sleepiness in the elderly.This extreme drowsiness may cause you to eat or drink less than you normally would. Tell your doctor if you are not able to eat or drink as you normally do. Your doctor may start you at a lower dose of valproic acid oral solution.

Call your healthcare provider right away, if you have any of the symptoms listed above.

The common side effects of valproic acid oral solution include:

- nausea
- headache
- sleepiness
- vomiting
- weakness
- tremor
- dizziness
- stomach pain
- blurry vision
- double vision
- diarrhea
- increased appetite
- weight gain
- hair loss
- loss of appetite
- problems with walking or coordination

These are not all of the possible side effects of valproic acid oral solution. For more information, ask your healthcare provider or pharmacist.

Tell your healthcare provider if you have any side effect that bothers you or that does not go away.

Call your doctor for medical advice about side effects. You may report side effects to FDA at 1-800-FDA-1088.

How should I store valproic acid oral solution?

- Store valproic acid oral solution at 68° to 77°F (20° to 25°C).

Keep valproic acid oral solution and all medicines out of the reach of children.

General information about the safe and effective use of valproic acid oral solution

Medicines are sometimes prescribed for purposes other than those listed in a Medication Guide. Do not use valproic acid oral solution for a condition for which it was not prescribed. Do not give valproic acid oral solution to other people, even if they have the same symptoms that you have. It may harm them.

This Medication Guide summarizes the most important information about valproic acid oral solution. If you would like more information, talk with your healthcare provider. You can ask your pharmacist or healthcare provider for information about valproic acid oral solution that is written for health professionals.

What are the ingredients in valproic acid oral solution?

Active ingredient: valproic acid

Inactive ingredients: alchohol (less than 0.05%), artificial cherry flavor, artificial wild cherry flavor, corn syrup solids, FD&C Red No. 40, glycerin, hydrochloric acid, liquid sugar, methylparaben, potassium phosphate dibasic, propylene glycol, purified water, sodium benzoate and sodium hydroxide

This Medication Guide has been approved by the U.S. Food and Drug Administration.

Rx Only

Product No.: 4021

Manufactured By:

Xttrium Laboratories, Inc.

Mount Prospect, IL 60056

4021VALINST

REV. 06-25

PACKAGE LABEL

Product No.: 4021

Manufactured By:

Xttrium Laboratories, Inc.

Mount Prospect, IL 60056

4021VALINST

REV. 06-25

PACKAGE LABEL.PRINCIPAL DISPLAY PANEL

NDC 0116-4021-16

VALPROIC ACID ORAL SOLUTION, USP

250 mg/5 mL

Alcohol less than 0.05%

Each 5mL (teaspoonful) contains the equivalent of 250 mg Valproic Acid, USP (as the sodium salt) and less than 0.05% alcohol contributed by flavorings.

PHARMACIST: PLEASE DISPENSE THE ACCOMPANYING MEDICATION GUIDE TO EACH PATIENT.

Rx Only

NET: 1 Pint (480 mL)

USUAL DOSAGE: See accompanying package insert for full prescribing information.

WARNINGS: KEEP THIS AND ALL DRUGS OUT OF REACH OF CHILDREN. In case of accidental overdose, seek professional assistance or contact a Poison Control Center immediately.

Store at 20° - 25°C (68° - 77°F). [See USP Controlled Room Temperature].

Dispense in a tight, light-resistant container as defined in the USP, with child-resistant closure.

Manufactured by:

Xttrium Laboratories, Inc.

1200 E. Business Center Dr.

Mount Prospect, IL 60056

4021VALP16LBL

REV. 06-25

PACKAGE LABEL

UNIT DOSE

Delivers 5 mL

NDC 0116-4021-05

Valproic Acid

Oral Solution USP,

250 mg/5 mL

Rx Only

Xttrium Laboratories, Inc.

Mount Prospect

IL 60056

SEE INSERT

4021VAL05LID

PACKAGE LABEL

UNIT DOSE

Delivers 10 mL

NDC 0116-4021-10

Valproic Acid Oral Solution USP,

500 mg/10 mL

Rx Only

Xttrium Laboratories, Inc.

Mount Prospect

IL 60056

SEE INSERT

4021VAL10LID